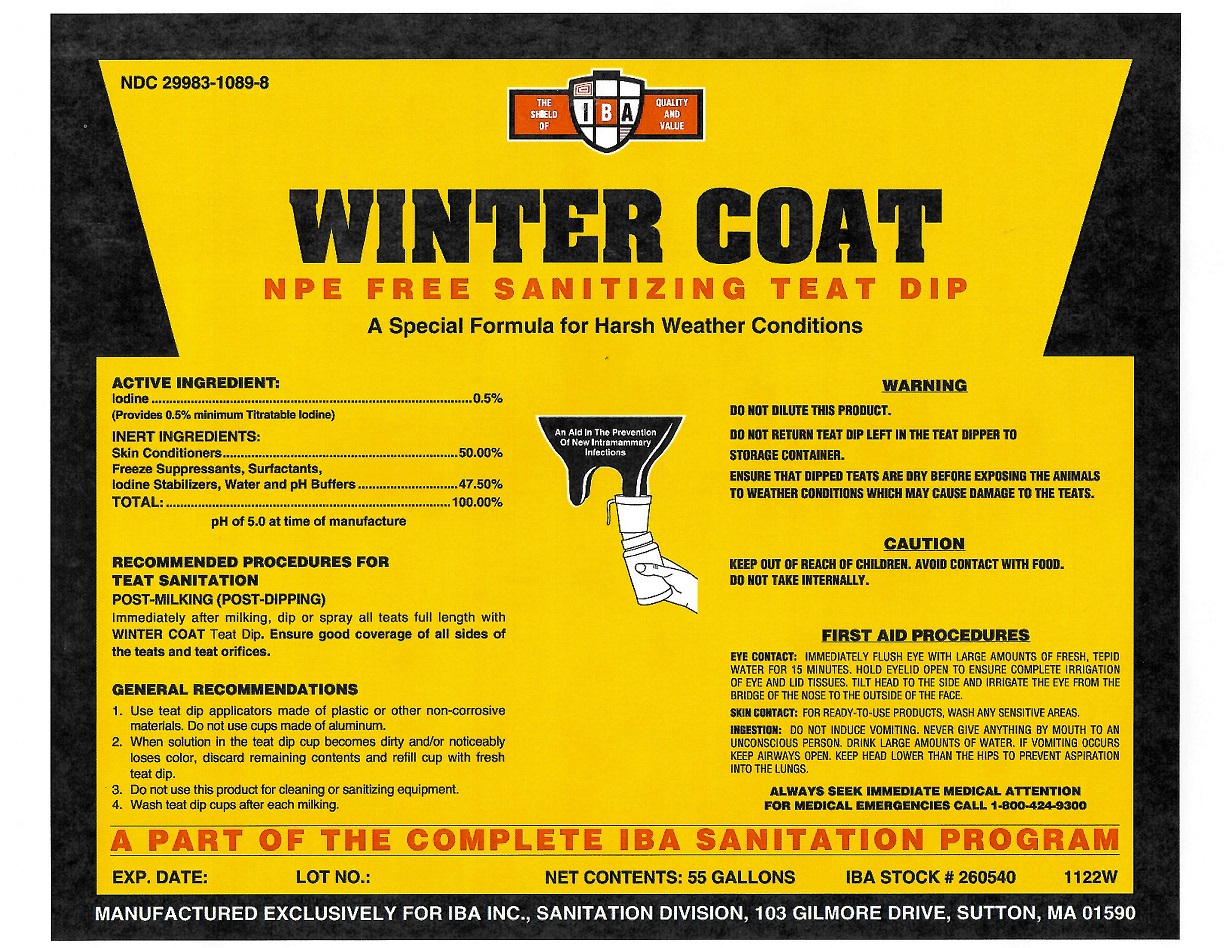 DRUG LABEL: Winter Coat NPE Free
NDC: 29983-1089 | Form: LIQUID
Manufacturer: IBA
Category: animal | Type: OTC ANIMAL DRUG LABEL
Date: 20251211

ACTIVE INGREDIENTS: IODINE .50 kg/100 kg

Winter Coat NPE Free

Active Ingredient

Iodine 0.5%

Inert Ingredients

Skin Conditioners, Freeze Supressants, Surfactants, Iodine Stabliizers, Water and pH Buffers

RECOMMENDED PROCEDURES FOR TEAT SANITATION

POST-MILKING (POST-DIPPING)

Immediately after milking, dip or spray all teats full length with WINTER COAT Teat Dip. Ensure good coverage of all sides of the teats and teats orifices.

GENERAL RECOMMENDATIONS

1. Use teat dip applicators made of plastic or other non-corrosive materials. Do not use cups made of aluminum.

2. When solution in the teat dip cup becomes dirty and/or noticebly loses color, discard remaining contents and refill cup with fresh teat dip.

3. Do not use this product for cleaning or sanitizing equipment.

4. Wash teat dip cups after each milking.

WARNING

DO NOT DILUTE THIS PRODUCT.

DO NOT RETURN TEAT DIP LEFT IN THE TEAT DIPPER TO STORAGE CONTAINER.

ENSURE THAT DIPPED TEATS ARE DRY BEFORE EXPOSING THE ANIMALS TO WEATHER CONDITIONS WHICH MAY CAUSE DAMAGE TO THE TEATS.

CAUTION

KEEP OUT OF REACH OF CHILDREN. AVOID CONTACT WITH FOOD.

DO NOT TAKE INTERNALLY.

FIRST AID PROCEDURES

EYE CONTACT: IMMEDIATELY FLUSH EYE WITH LARGE AMOUNTS OF FRESH TEPID WATER FOR 15 MINUTES. HOLD EYELID OPEN TO ENSURE COMPLETE IRRIGATION OF EYE AND LID TISSUES. TILT HEAD TO THE SIDE AND IRRIGATE THE EYE FROM THE BRIDGE OF THE NOSE TO THE OUTSIDE OF THE FACE.

SKIN CONTACT: FOR READY-TO-USE PRODUCTS, WASH ANY SENSITIVE AREAS.

INGESTION: DO NOT INDUCE VOMITING. NEVER GIVE ANYTHING BY MOUTH TO AN UNCONSCIOUS PERSON. DRINK LARGE AMOUNTS OF WATER. IF VOMITING OCCURS KEEP AIRWAYS OPEN. KEEP HEAD LOWER THAN THE HIPS TO PREVENT ASPIRATION INTO THE LUNGS.

ALWAYS SEEK IMMEDIATE MEDICAL ATTENTION

FOR MEDICAL EMERGENCIES CALL 1-800-424-9300